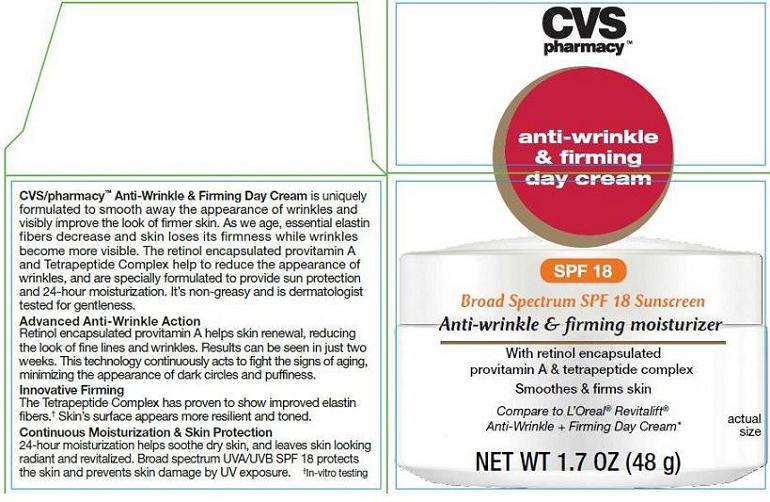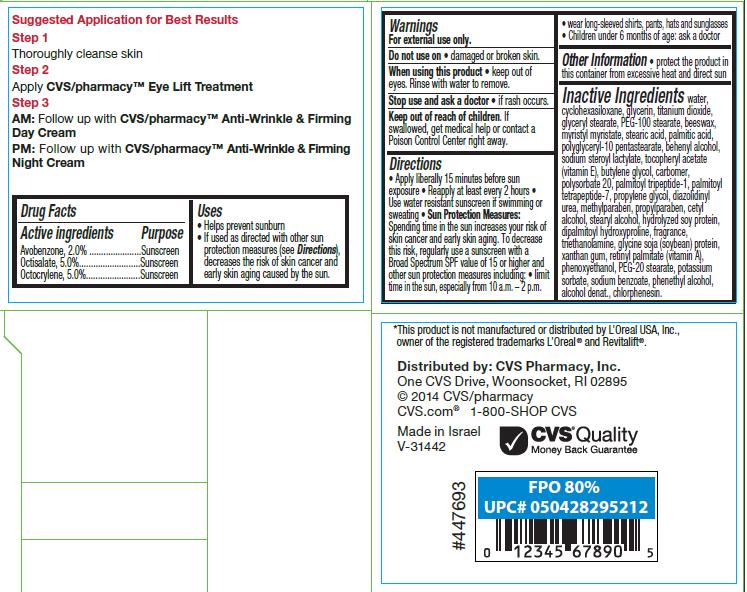 DRUG LABEL: ANTI-WRINKLE AND FIRMING BROAD SPECTRUM SPF18 SUNSCREEN
NDC: 59779-378 | Form: CREAM
Manufacturer: CVS Pharmacy
Category: otc | Type: HUMAN OTC DRUG LABEL
Date: 20140521

ACTIVE INGREDIENTS: AVOBENZONE 2 g/100 g; OCTISALATE 5 g/100 g; OCTOCRYLENE 5 g/100 g
INACTIVE INGREDIENTS: WATER; CYCLOMETHICONE 6; GLYCERIN; TITANIUM DIOXIDE; GLYCERYL MONOSTEARATE; PEG-100 STEARATE; ROYAL JELLY; MYRISTYL MYRISTATE; STEARIC ACID; PALMITIC ACID; POLYGLYCERYL-10 STEARATE; DOCOSANOL; SODIUM STEAROYL LACTYLATE; .ALPHA.-TOCOPHEROL ACETATE; BUTYLENE GLYCOL; CARBOMER COPOLYMER TYPE A (ALLYL PENTAERYTHRITOL CROSSLINKED); POLYSORBATE 20; PALMITOYL TETRAPEPTIDE-7; PROPYLENE GLYCOL; DIAZOLIDINYL UREA; METHYLPARABEN; PROPYLPARABEN; CETYL ALCOHOL; STEARYL ALCOHOL; SOY PROTEIN; DIPALMITOYL HYDROXYPROLINE; TROLAMINE; SOY STEROL; XANTHAN GUM; VITAMIN A PALMITATE; PHENOXYETHANOL; PEG-20 STEARATE; POTASSIUM SORBATE; SODIUM BENZOATE; PHENYLETHYL ALCOHOL; ALCOHOL; CHLORPHENESIN

CVS pharmacy™ anti-wrinkle & firming day cream

Active ingredient

Avobenzone, 2.0%
Oclisalate, 5.0%
Octocrylene, 5.0%

Purpose

Sunscreen

Uses

- Helps prevent sunburn
- If used as directed with other sun protection measures (see Directions), decreases the risk of skin cancer and early skin aging caused by the sun

Warnings

For external use only.

Do not use on

- damaged or broken skin.

When using this product

- keep out of eyes. Rinse with water to remove.

Stop use and ask a doctor

- if rash occurs.

Keep out of reach of children.

If swallowed, get medical help or contact a Poison Control Center right away.

Directions

- Apply liberally 15 minutes before sun exposure
- Reapply at least every 2 hours
- Use water-resistant sunscreen if swimming or sweating
- Sun Protection Measures: Spending time in the sun increases your risk of skin cancer and early skin aging. To decrease this risk, regularly use a sunscreen with a Broad Spectrum SPF value of 15 or higher and other sun protection measures including:
  - limit time in the sun, especially from 10 a.m. - 2 p.m.
  - wear long-sleeved shirts, pants, hats and sunglasses
- Children under 6 months: ask a doctor

Other Information

- protect the product in this container from excessive heat and direct sun

Inactive Ingredients

water, cyclopentasiloxane, glycerin, titanium dioxide, glyceryl stearate, PEG-100 stearate, beeswax, myristyl myristate, stearic acid, palmitic acid, polyglyceryl-10 pentastearate, behenyl alcohol, sodium steroyl lactylate, tocopheryl acetate (vitamin E), butylene glycol, carbomer, polysorbate 20, palmitoyl tripeptide-1, palmitoyl tetrapeptide-7, propylene glycol, diazolidinyl urea, methylparaben, propylparaben, cetyl alcohol, stearyl alcohol, hydrolyzed soy protein, dipalmitoyl hydroxyproline, fragrance, triethanolamine, glycine soja (soybean) protein, xanthan gum, retinyl palmitate (vitamin A), phenoxyethanol, PEG-20 stearate, potassium sorbate, sodium benzoate, phenethyl alcohol, alcohol denat., chlorphenesin.

Package/Label Principal Display Panel - Carton Label

CVS pharmacy™
anti-wrinkle & firming day cream
SPF 18
Broad Spectrum SPF 18 Sunscreen
Anti-wrinkle & firming moisturizer

With retinol encapsulated provitamin A & tetrapepitide complex

Smooths & firms skin

Compare to L’Oreal® Revitalift® Anti-Wrinkle + Firming Day Cream*

NET WT 1.7 OZ (49g)

CVS/pharmacy™ Anti-Wrinkle & Firming Day Cream is uniquely formulated to smooth away the appearance of wrinkles and visibly improve the look of firmer skin. As we age, essential elastin fibers decrease and skin loses its firmness while wrinkles become more visible. The retinol encapsulated provitamin A and Tetrapeptide Complex help to reduce the appearance of wrinkles, and are specially formulated to provide sun protection and 24-hour moisturization. It’s non-greasy and is dermatologist tested for gentleness.

Advanced Anti-Wrinkle Action
Retinol encapsulated provitamin A helps skin renewal, reducing the look of fine lines and wrinkles. Results can be seen in just two weeks. This technology continuously acts to fight the signs of aging, minimizing the appearance of dark circles and puffiness.

Innovative Firming
The Tetrapeptide Complex has proven to show improved elastin fibers.† Skin’s surface appears more resilient and toned.

Continuous Moisturization & Skin Protection
24-hour moisturization helps soothe dry skin, and leaves skin looking radiant and revitalized. Broad spectrum UVA/UVB SPF 18 protects the skin and prevents skin damage by UV exposure.

†In-vitro testing

*This product is not manufactured or distributed by L’Oreal USA, Inc., owner of the registered trademarks L’Oreal® and Revitalift®.

Distributed by: CVS Pharmacy, Inc.
One CVS Drive, Woonsocket, RI 02895
© 2014 CVS/pharmacy
CVS.com® 1-800-SHOP CVS

Made in Israel V-31442

CVS® Quality
Money Back Guarantee

Carton Label – Front

Carton Label - Back